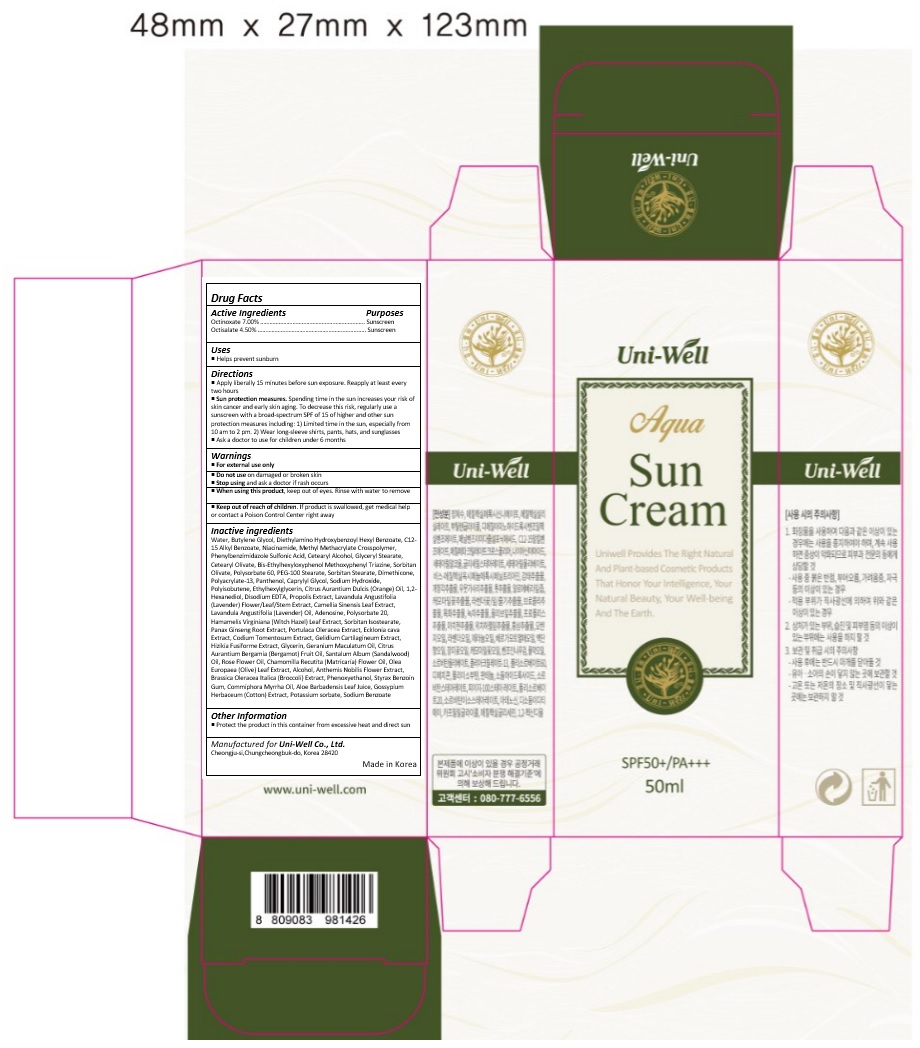 DRUG LABEL: UNIWELL AQUA SUNCREAM
NDC: 71502-001 | Form: CREAM
Manufacturer: uniwell LTD
Category: otc | Type: HUMAN OTC DRUG LABEL
Date: 20170612

ACTIVE INGREDIENTS: Octinoxate 3.5 mg/50 mL; OCTISALATE 2.25 mg/50 mL
INACTIVE INGREDIENTS: WATER; Butylene Glycol; DIETHYLAMINO HYDROXYBENZOYL HEXYL BENZOATE; ALKYL (C12-15) BENZOATE; NIACINAMIDE; ENSULIZOLE; CETOSTEARYL ALCOHOL; GLYCERYL MONOSTEARATE; Cetearyl Olivate; BEMOTRIZINOL; Sorbitan Olivate; Polysorbate 60; PEG-100 Stearate; SORBITAN MONOSTEARATE; DIMETHICONE; POLYACRYLAMIDE (1500 MW); Panthenol; Caprylyl Glycol; Sodium Hydroxide; POLYISOBUTYLENE (1000 MW); Ethylhexylglycerin; ORANGE OIL; 1,2-Hexanediol; EDETATE DISODIUM ANHYDROUS; PROPOLIS WAX; LAVANDULA ANGUSTIFOLIA SUBSP. ANGUSTIFOLIA FLOWERING TOP; GREEN TEA LEAF; LAVENDER OIL; ADENOSINE; POLYSORBATE 20; HAMAMELIS VIRGINIANA LEAF; SORBITAN ISOSTEARATE; ASIAN GINSENG; PURSLANE; ECKLONIA CAVA; CODIUM TOMENTOSUM; GELIDIUM CARTILAGINEUM; SARGASSUM FUSIFORME; Glycerin; GERANIUM MACULATUM ROOT OIL; BERGAMOT OIL; SANDALWOOD OIL; ROSA RUGOSA FLOWER BUD; CHAMOMILE FLOWER OIL; OLEA EUROPAEA LEAF; Alcohol; CHAMAEMELUM NOBILE FLOWER; PHENOXYETHANOL; STYRAX BENZOIN RESIN; MYRRH OIL; ALOE VERA LEAF; LEVANT COTTON SEED; POTASSIUM SORBATE; SODIUM BENZOATE

Drug Facts

ACTIVE INGREDIENT

OCTINOXATE 7.00%

OCTISALATE 4.50%

PURPOSE

Sunscreen

INDICATIONS AND USAGE

Helps prevent sunburn

DOSAGE AND ADMINISTRATION

Apply liberally 15 minutes before sun exposure.

Reapply at least every two hours

Sun protection measures. Spending time in the sun increases your risk of skin cancer and early skin aging. To decrease this risk, regularly use a sunscreen with a broad spectrum SPF of 15 of higher and other sun protection measures including: 1) Limited time in the sun, especially from 10 am to 2 pm. 2) Wear long-sleeve shirts, pants, hats, and sunglasses
Ask a doctor to use for children under 6 months

WARNINGS

For external use only.
Do not use on damaged or broken skin.
When using this product, keep out of eyes. Rinse with water to remove.
Stop using and ask a doctor if rash occurs.

KEEP OUT OF REACH OF CHILDREN

Keep out of reach of the children. If product is swallowed, get medical help or contact a poison control center right away.

INACTIVE INGREDIENT

Water, Butylene Glycol, Diethylamino Hydroxybenzoyl Hexyl Benzoate, C12-15 Alkyl Benzoate, Niacinamide, Methyl Methacrylate Crosspolymer, Phenylbenzimidazole Sulfonic Acid, Cetearyl Alcohol, Glyceryl Stearate, Cetearyl Olivate, Bis-Ethylhexyloxyphenol Methoxyphenyl Triazine, Sorbitan Olivate, Polysorbate 60, PEG-100 Stearate, Sorbitan Stearate, Dimethicone, Polyacrylate-13, Panthenol, Caprylyl Glycol, Sodium Hydroxide, Polyisobutene, Ethylhexylglycerin, Citrus Aurantium Dulcis (Orange) Oil, 1,2-Hexanediol, Disodium EDTA, Propolis Extract, Lavandula Angustifolia (Lavender) Flower/Leaf/Stem Extract, Camellia Sinensis Leaf Extract, Lavandula Angustifolia (Lavender) Oil, Adenosine, Polysorbate 20, Hamamelis Virginiana (Witch Hazel) Leaf Extract, Sorbitan Isostearate, Panax Ginseng Root Extract, Portulaca Oleracea Extract, Ecklonia cava Extract, Codium Tomentosum Extract, Gelidium Cartilagineum Extract, Hizikia Fusiforme Extract, Glycerin, Geranium Maculatum Oil, Citrus Aurantium Bergamia (Bergamot) Fruit Oil, Santalum Album (Sandalwood) Oil, Rose Flower Oil, Chamomilla Recutita (Matricaria) Flower Oil, Olea Europaea (Olive) Leaf Extract, Alcohol, Anthemis Nobilis Flower Extract, Brassica Oleracea Italica (Broccoli) Extract, Phenoxyethanol, Styrax Benzoin Gum, Commiphora Myrrha Oil, Aloe Barbadensis Leaf Juice, Gossypium Herbaceum (Cotton) Extract, Potassium sorbate, Sodium Benzoate